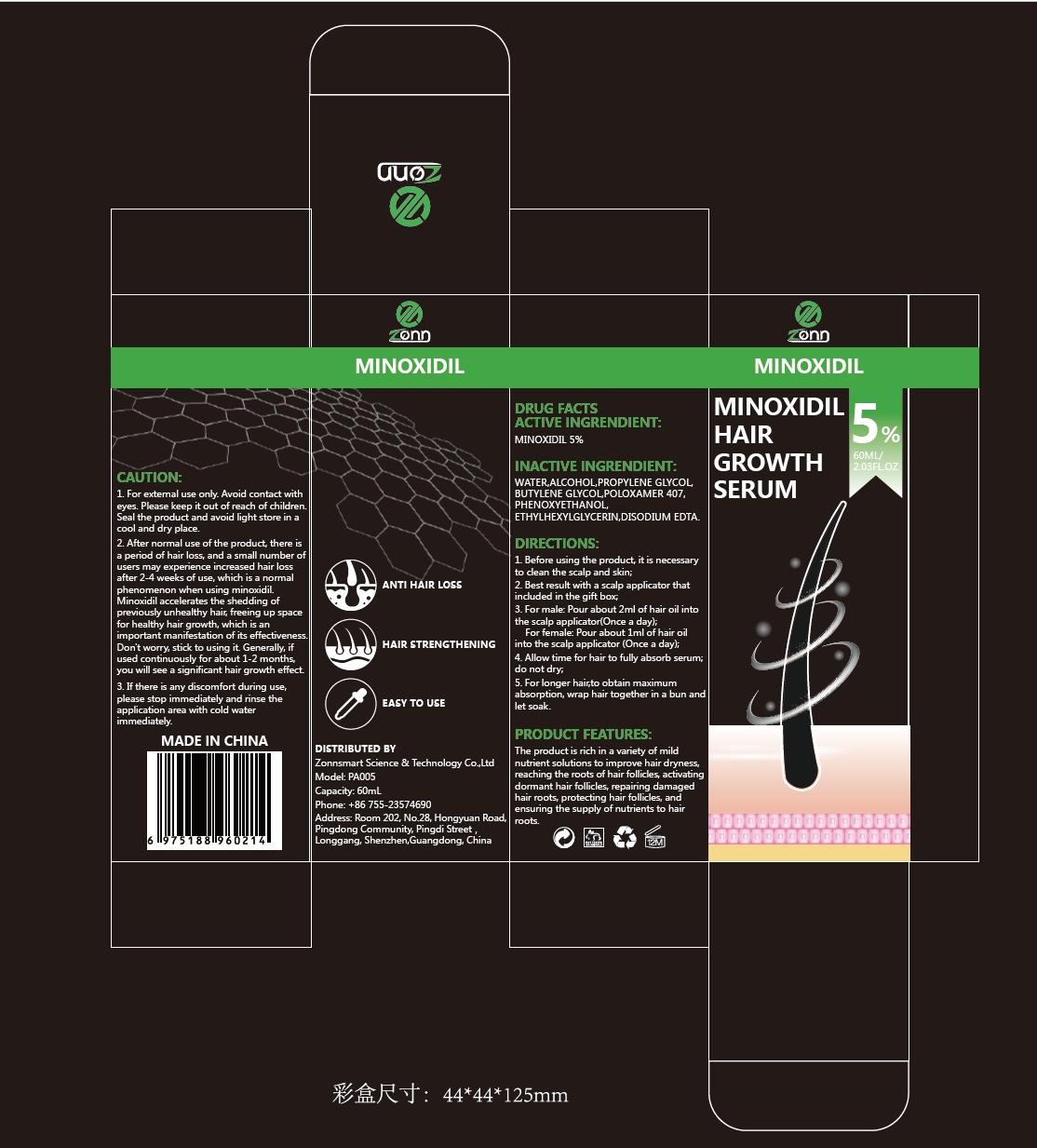 DRUG LABEL: 5% Minoxidil hair growth serum
NDC: 84693-002 | Form: LIQUID
Manufacturer: Zonnsmart Science & Technology Co.,Ltd
Category: otc | Type: HUMAN OTC DRUG LABEL
Date: 20240830

ACTIVE INGREDIENTS: MINOXIDIL 5 g/100 mL
INACTIVE INGREDIENTS: WATER; ETHYLHEXYLGLYCERIN; PHENOXYETHANOL; POLOXAMER 407; PROPYLENE GLYCOL; BUTYLENE GLYCOL; DISODIUM EDTA-COPPER; BENZYL ALCOHOL

5% Minoxidil hair growth serum

ACTIVE INGREDIENT

MINOXIDIL 5%

PURPOSE

ANTI HAIR LOSS, HAIR STRENGTHENING

Please keep it out of reach of children.

INDICATIONS AND USAGE

ANTI HAIR LOSS, HAIR STRENGTHENING, EASY TO USE

WARNINGS

1. For extemal use only, Avoid contact witheyes. Please keep it out of reach of children. Seal the product and avoid light store in acool and dry place.

DOSAGE AND ADMINISTRATION

1. Before using the product, it is necessaryto clean the scalp and skin;
2. Best result with a scalp applicator thatincluded in the gift box
3. For male: Pour about 2ml of hair oil intothe scalp applicator(Once a day);For female: Pour about lml of hair oilinto the scalp applicator (Once a day);
4. Allow time for hair to fully absorb serum;do not dry;
5. For longer hair,to obtain maximumabsorption, wrap hair together in a bun andlet soak.

STORAGE AND HANDLING

Seal the product and avoid light store in acool and dry place.

INACTIVE INGREDIENT

POLOXAMER 407
PHENOXYETHANOL
ETHYLHEXYLGLYCERIN
DISODIUM EDTA
WATER
ALCOHOL
PROPYLENE GLYCOL
BUTYLENE GLYCOL